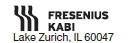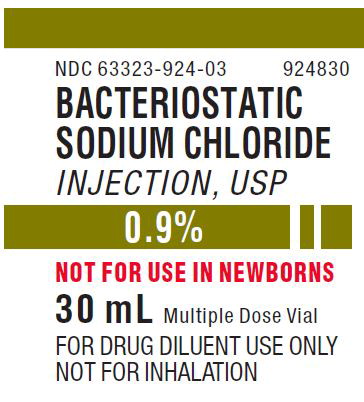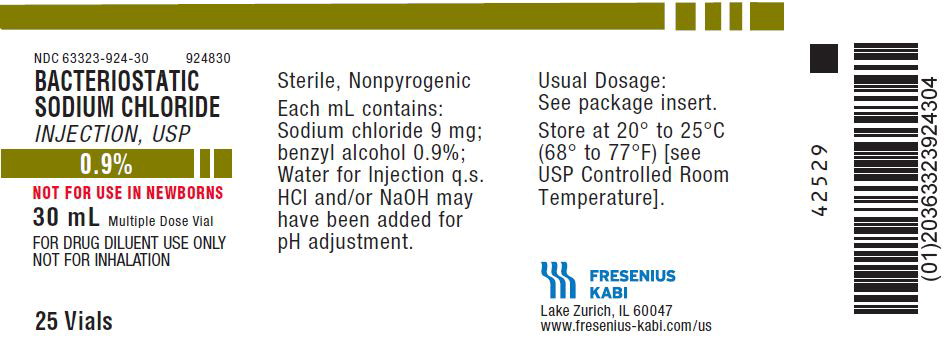 DRUG LABEL: Bacteriostatic Sodium Chloride
NDC: 63323-924 | Form: INJECTION
Manufacturer: Fresenius Kabi USA, LLC
Category: prescription | Type: HUMAN PRESCRIPTION DRUG LABEL
Date: 20241011

ACTIVE INGREDIENTS: SODIUM CHLORIDE 9 mg/1 mL
INACTIVE INGREDIENTS: BENZYL ALCOHOL; HYDROCHLORIC ACID; SODIUM HYDROXIDE

Bacteriostatic Sodium Chloride Injection, USP

0.9%

NOT FOR USE IN NEWBORNS

DESCRIPTION

Bacteriostatic Sodium Chloride Injection, USP, 0.9% is a sterile, nonpyrogenic, isotonic solution.

Each mL contains: Sodium chloride 9 mg; benzyl alcohol 0.9%; Water for Injection q.s. Hydrochloric acid and/or sodium hydroxide may have been added for pH adjustment (pH 4.5-7.0).

Sodium chloride occurs as colorless cubic crystals or white crystalline powder and has a saline taste. Sodium chloride is freely soluble in water. It is soluble in glycerin and slightly soluble in alcohol.

The empirical formula for sodium chloride is NaCl and the molecular weight is 58.44.

CLINICAL PHARMACOLOGY

Sodium chloride in water dissociates to provide sodium (Na^+) and chloride (Cl^-) ions. These ions are normal constituents of the body fluids (principally extracellular) and are essential for maintaining electrolyte balance.

The distribution and excretion of sodium (Na^+) and chloride (Cl^-) are largely under the control of the kidney which maintains a balance between intake and output.

The small volume of fluid and amount of sodium chloride provided by Bacteriostatic Sodium Chloride Injection, USP, 0.9%, when used only as a vehicle for parenteral injection of drugs, is unlikely to exert a significant effect on fluid and electrolyte balance except possibly in very small infants.

Water is an essential constituent of all body tissues and accounts for approximately 70% of total body weight. Average normal adult daily requirement ranges from two to three liters (1 to 1.5 liters each of insensible water loss by perspiration and urine production).

Water balance is maintained by various regulatory mechanisms. Water distribution depends primarily on the concentration of electrolytes in the body compartments and sodium (Na^+) plays a major role in maintaining physiologic equilibrium.

INDICATIONS AND USAGE

These parenteral preparations are indicated only for diluting or dissolving drugs for intravenous, intramuscular or subcutaneous injection, according to instructions of the manufacturer of the drug to be administered. NOT FOR INHALATION.

CONTRAINDICATIONS

Due to potential toxicity of benzyl alcohol in newborns, Bacteriostatic Sodium Chloride Injection, USP, 0.9% containing benzyl alcohol must not be used in this patient population.

Bacteriostatic Sodium Chloride Injection, USP, 0.9% should not be used for fluid or sodium chloride replacement.

WARNINGS

Benzyl alcohol as a preservative in Bacteriostatic Sodium Chloride Injection, USP, 0.9% has been associated with toxicity in newborns. Data is unavailable on the toxicity of other preservatives in this age group. Preservative-free Sodium Chloride Injection, USP, 0.9% should be used for flushing intravascular catheters. Where a sodium chloride solution is required for preparing or diluting medications for use in newborns, only preservative-free Sodium Chloride Injection, USP, 0.9% should be used.

PRECAUTIONS

General

Bacteriostatic Sodium Chloride Injection, USP, 0.9% should not be used for those medicinals that specify the use of only Sodium Chloride Injection, USP, 0.9% as a sterile solvent.

Sodium chloride must be used with caution in the presence of congestive heart failure, circulatory insufficiency, kidney dysfunction or hypoproteinemia.

Excessive amounts of sodium chloride by any route may cause hypopotassemia and acidosis. Excessive amounts by the parenteral route may precipitate congestive heart failure and acute pulmonary edema, especially in patients with cardiovascular disease and in patients receiving corticosteroids or corticotropin or drugs that may give rise to sodium retention.

Pregnancy

Pregnancy Category C—

Animal reproduction studies have not been conducted with Bacteriostatic Sodium Chloride Injection, USP, 0.9%. It is also not known whether Bacteriostatic Sodium Chloride Injection, USP, 0.9% can cause fetal harm when administered to a pregnant woman or can affect reproduction capacity. Bacteriostatic Sodium Chloride Injection, USP, 0.9% should be given to a pregnant woman only if clearly needed.

ADVERSE REACTIONS

To report SUSPECTED ADVERSE REACTIONS, contact Fresenius Kabi USA, LLC at 1-800-551-7176 or FDA at 1-800-FDA-1088 or www.fda.gov/medwatch.

Reactions which may occur because of Bacteriostatic Sodium Chloride Injection, USP, 0.9%, added drugs or the technique of reconstitution or administration include febrile response, local tenderness, abscess, tissue necrosis or infection at the site of injection, venous thrombosis or phlebitis extending from the site of injection and extravasation.

If an adverse reaction does occur, discontinue the infusion, evaluate the patient, institute appropriate countermeasures and if possible, retrieve and save the remainder of the unused vehicle for examination.

Although adverse reactions to intravenous, intramuscular or subcutaneous injection of 0.9% benzyl alcohol are not known to occur in man, experimental studies of small volume parenteral preparations containing 0.9% benzyl alcohol in several species of animals have indicated that an estimated intravenous dose up to 30 mL may be safely given to an adult without toxic effects. Administration of an estimated 9 mL to a 6 kg infant is potentially capable of producing blood pressure changes.

OVERDOSAGE

Use only as a diluent or solvent. This parenteral preparation is unlikely to pose a threat of sodium chloride or fluid overload except possibly in very small infants. In the event these should occur, reevaluate the patient and institute appropriate corrective measures. See PRECAUTIONS and ADVERSE REACTIONS.

DOSAGE AND ADMINISTRATION

NOT FOR INHALATION. Before Bacteriostatic Sodium Chloride Injection, USP, 0.9% is used as a vehicle for the administration of a drug, specific references should be checked for any possible incompatibility with sodium chloride or benzyl alcohol.

The volume of the preparation to be used for diluting or dissolving any drug for injection is dependent on the vehicle concentration, dose and route of administration as recommended by the manufacturer.

Isotonic solutions may be given subcutaneously, intravenously, and occasionally, intramuscularly.

Use Bacteriostatic Sodium Chloride Injection, USP, 0.9% with due regard for the compatibility of the benzyl alcohol it contains with the particular medicinal substance that is to be dissolved or diluted.

Parenteral drug products should be inspected visually for particulate matter and discoloration prior to administration, whenever solution and container permit.

HOW SUPPLIED

Bacteriostatic Sodium Chloride Injection, USP, 0.9%, preserved with benzyl alcohol is available as follows:

Product Code | Unit of Sale | Strength | Each
924810 | NDC 63323-924-10 Unit of 25 | 0.9% | NDC 63323-924-01 10 mL Multiple Dose Plastic Vial
924830 | NDC 63323-924-30 Unit of 25 | 0.9% | NDC 63323-924-03 30 mL Multiple Dose Plastic Vial

Use only if solution is clear and seal intact.

Store at 20° to 25°C (68° to 77°F) [see USP Controlled Room Temperature].

www.fresenius-kabi.com/us

45765E

Revised: September 2019

PACKAGE LABEL

PACKAGE LABEL - PRINCIPAL DISPLAY - Bacteriostatic Sodium Chloride 30 mL Multiple Dose Vial Label

NDC 63323-924-03 924830

Bacteriostatic Sodium Chloride Injection, USP

0.9%

NOT FOR USE IN NEWBORNS

30 mL Multiple Dose Vial

For Drug Diluent Use Only

Not for Inhalation

PACKAGE LABEL

PACKAGE LABEL – PRINCIPAL DISPLAY - Bacteriostatic Sodium Chloride 30 mL Multiple Dose Vial Tray Label

NDC 63323-924-30 924830

Bacteriostatic Sodium Chloride Injection, USP

0.9 %

NOT FOR USE IN NEWBORNS

30 mL Multiple Dose Vial

For Drug Diluent Use Only

Not for Inhalation

25 Vials